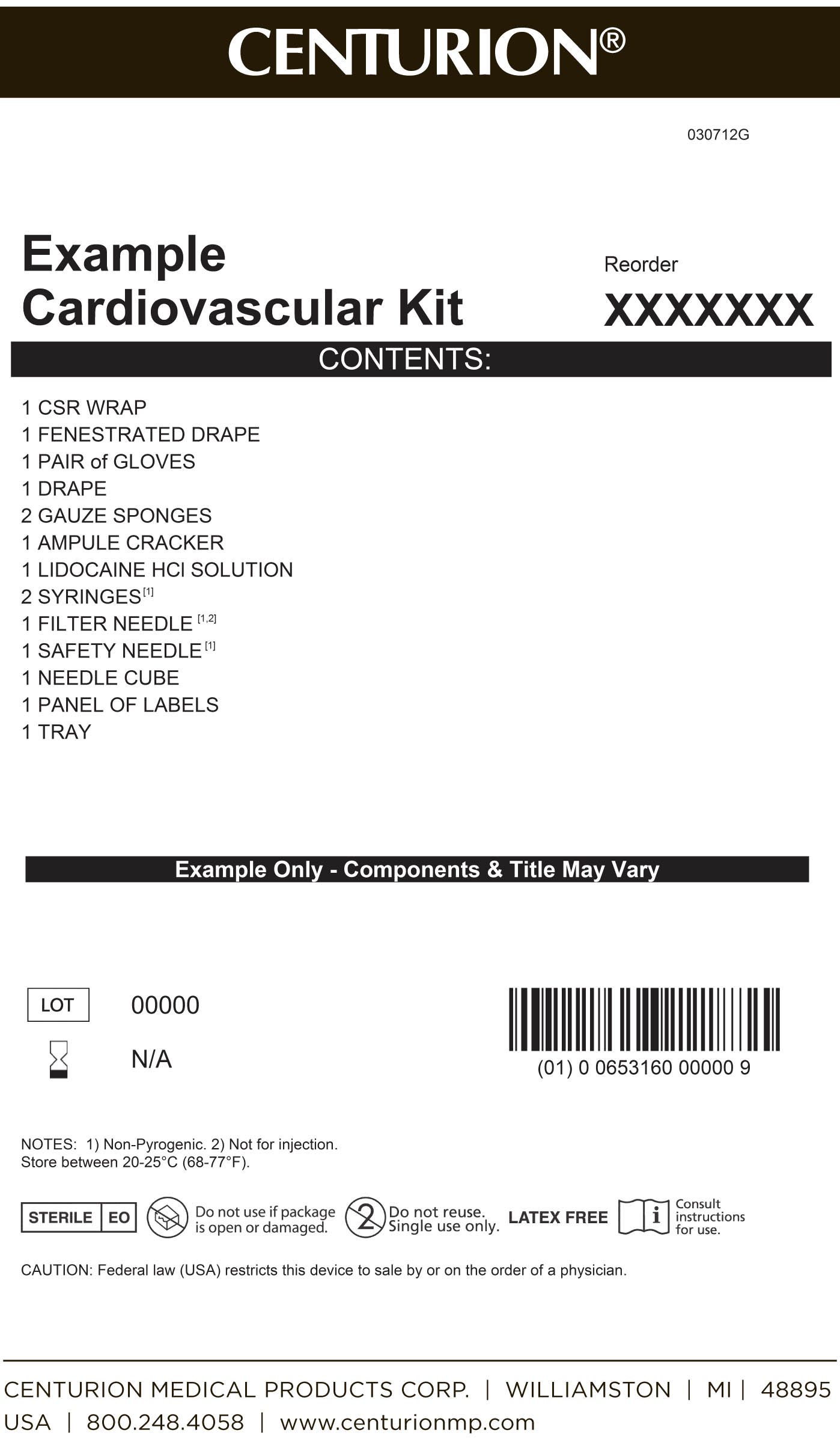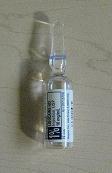 DRUG LABEL: Cardiovascular Procedure Kit
NDC: 24840-1101 | Form: KIT | Route: INFILTRATION
Manufacturer: Centurion Medical Products
Category: other | Type: MEDICAL DEVICE
Date: 20120604

ACTIVE INGREDIENTS: LIDOCAINE HYDROCHLORIDE ANHYDROUS 10 mg/1 mL
INACTIVE INGREDIENTS: SODIUM CHLORIDE 7 mg/1 mL; WATER; SODIUM HYDROXIDE; HYDROCHLORIC ACID

Cardiovascular Procedure Kit

DESCRIPTION

Lidocaine Hydrochloride Injection, USP is a sterile, nonpyrogenic solution of lidocaine hydrochloride in water for injection for parenteral administration in various concentrations. Multiple-dose vials contain 0.1% of methylparaben added as preservative. May contain sodium hydroxide and/or hydrochloric acid for pH adjustment. The pH is 6.5 (5.0 to 7.0). Lidocaine is a local anesthetic of the amide type. Lidocaine Hydrochloride, USP is a white powder freely soluable in water. The colecular weight is 288.82.

Cardiovascular Procedure Kit Primary Label

MM1

PACKAGE LABEL

MM1